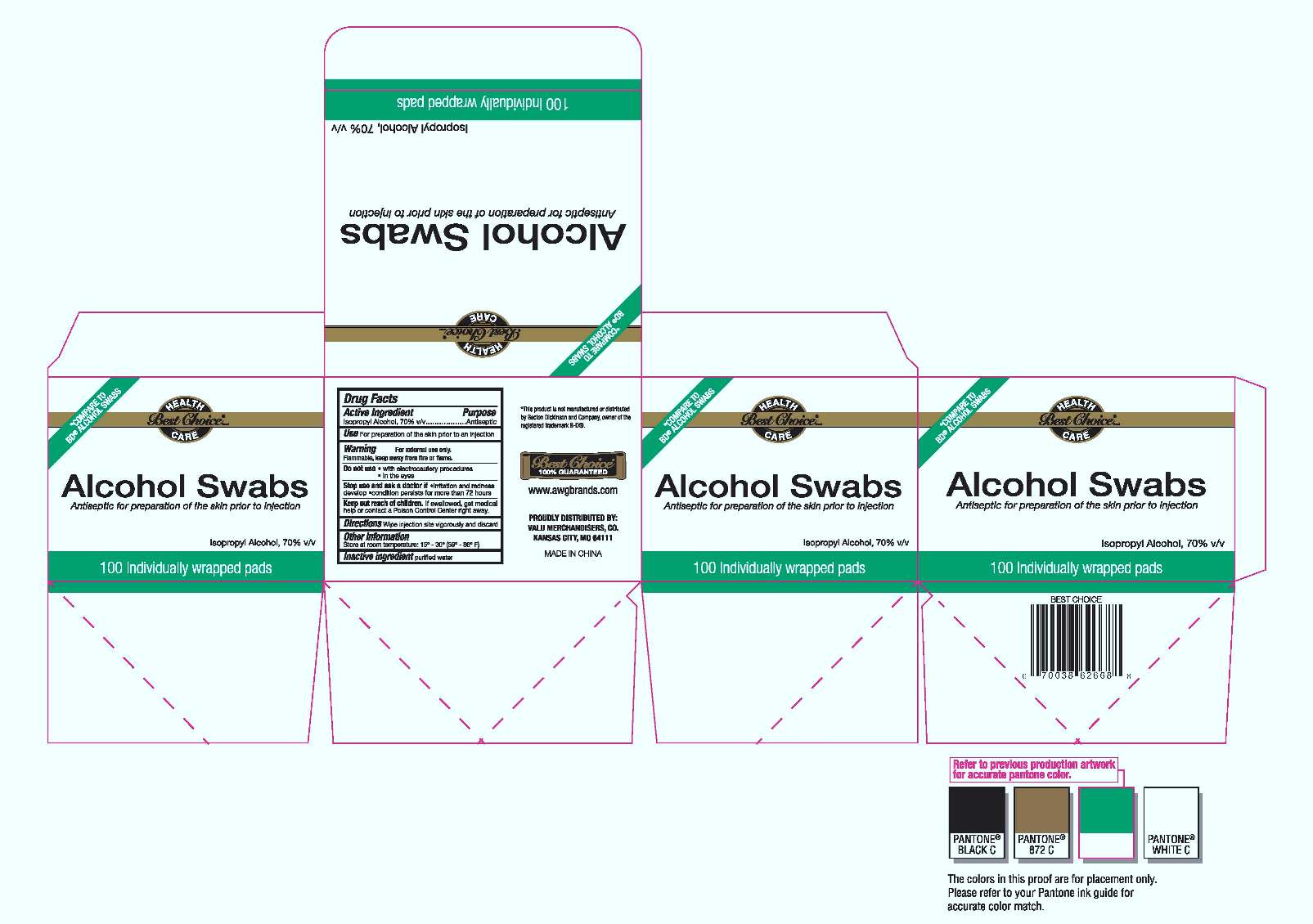 DRUG LABEL: Alcohol Prep Pad
NDC: 59229-005 | Form: SWAB
Manufacturer: YUYAO CHENGZE MEDICAL SUPPLIES FACTORY 
Category: otc | Type: HUMAN OTC DRUG LABEL
Date: 20130805

ACTIVE INGREDIENTS: ALCOHOL 70 mL/100 mL
INACTIVE INGREDIENTS: water 30 mL/100 mL

Alcohol Prep Pad

Active Ingredient

Isopropyl Alcohol 70%

Purpose

Antiseptic

Use

For preparation of skin prior to an injection

Warnning

For External use only.

Flammabel,keep away from fire or flame

Do not use

- with electrocautery procedures,
- in the eyes,

stop use if irritation and redness develop.

Ask a doceor if condition persists for more than 72 hours

Keep out of reach of children except with adult supervision.

If swallowed,get medical help or contact a Poison Control Center right away.

Directions

wipe injection site vigorously and discard

Other informaiton store at room temperature

Inactive Ingredients

Inactive Ingredients: Water